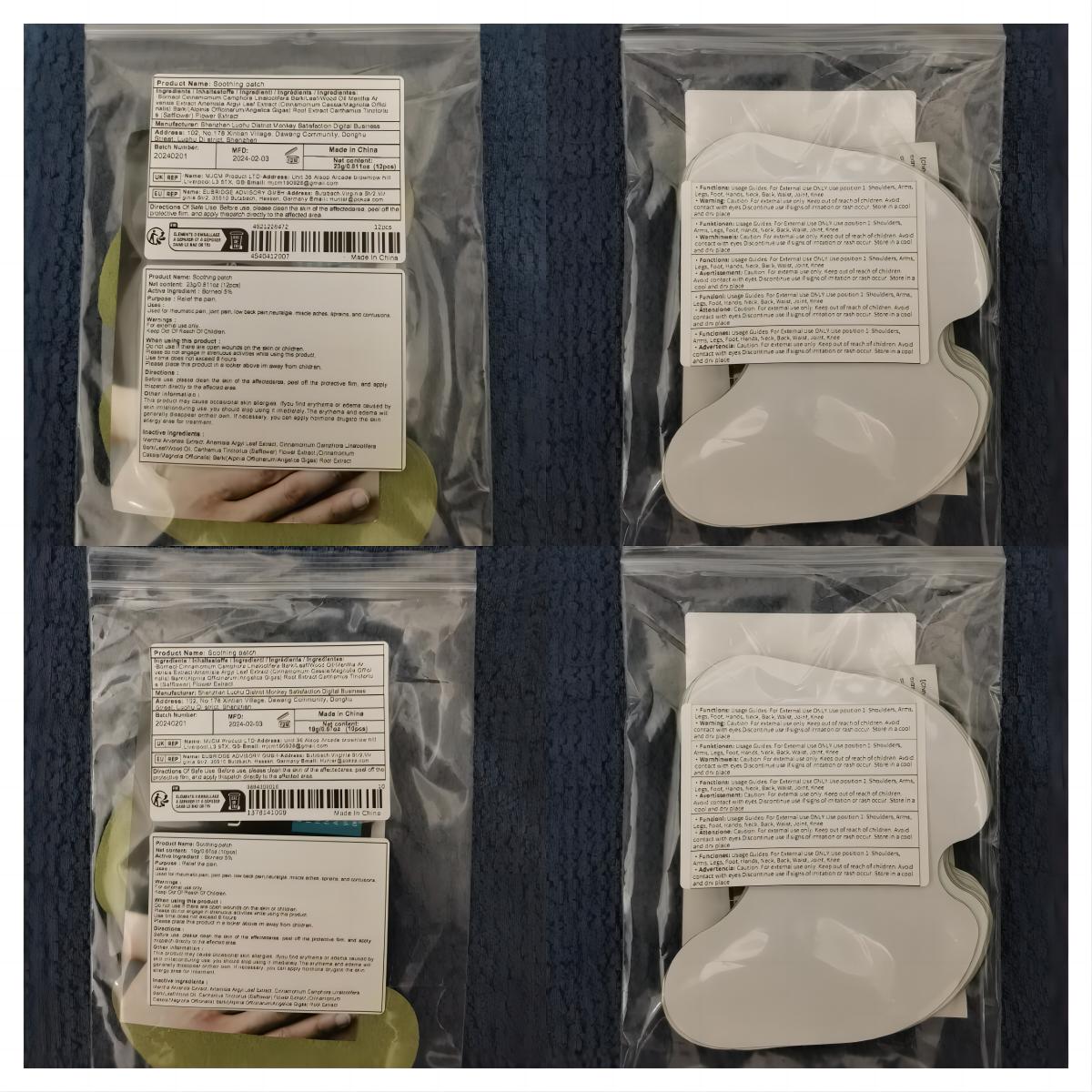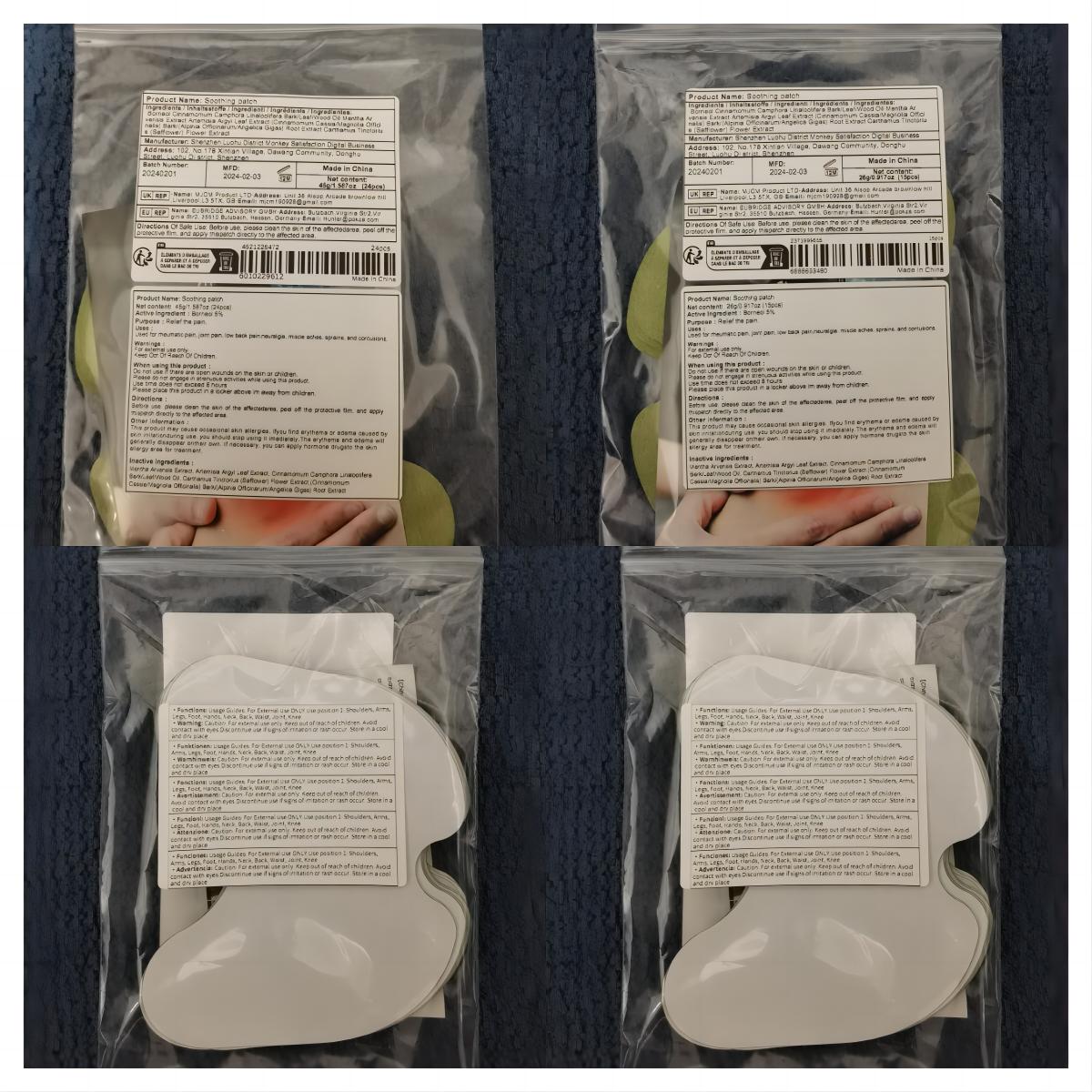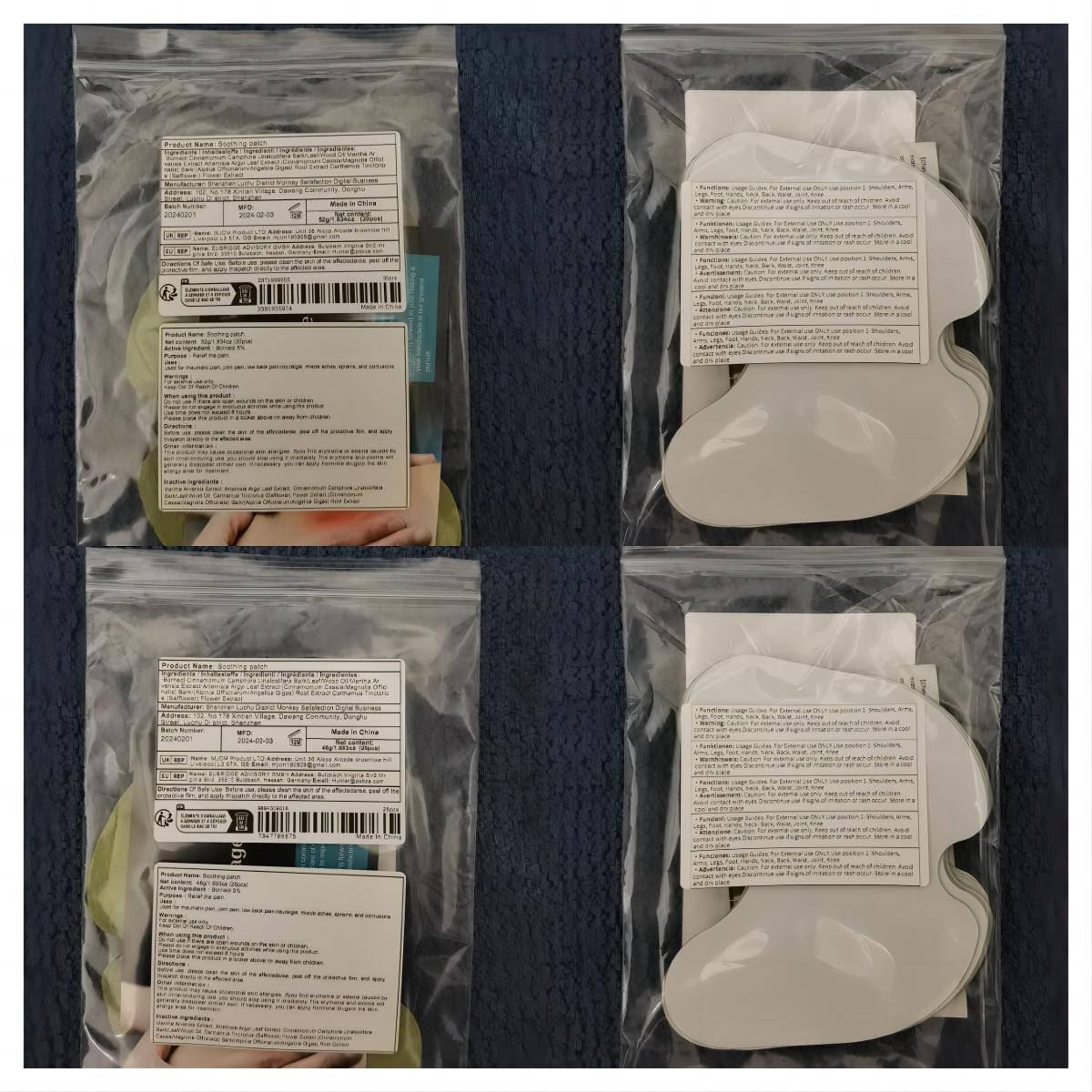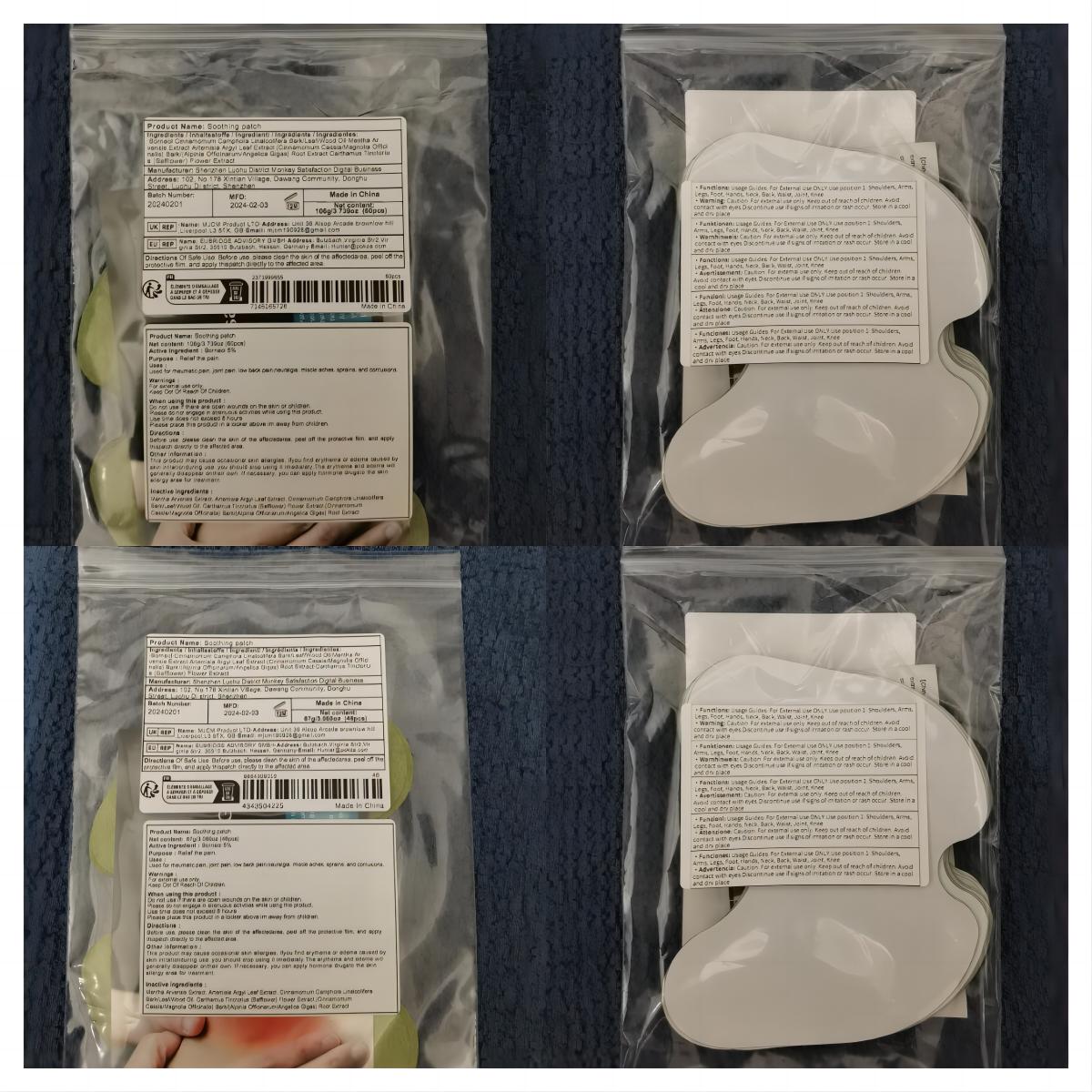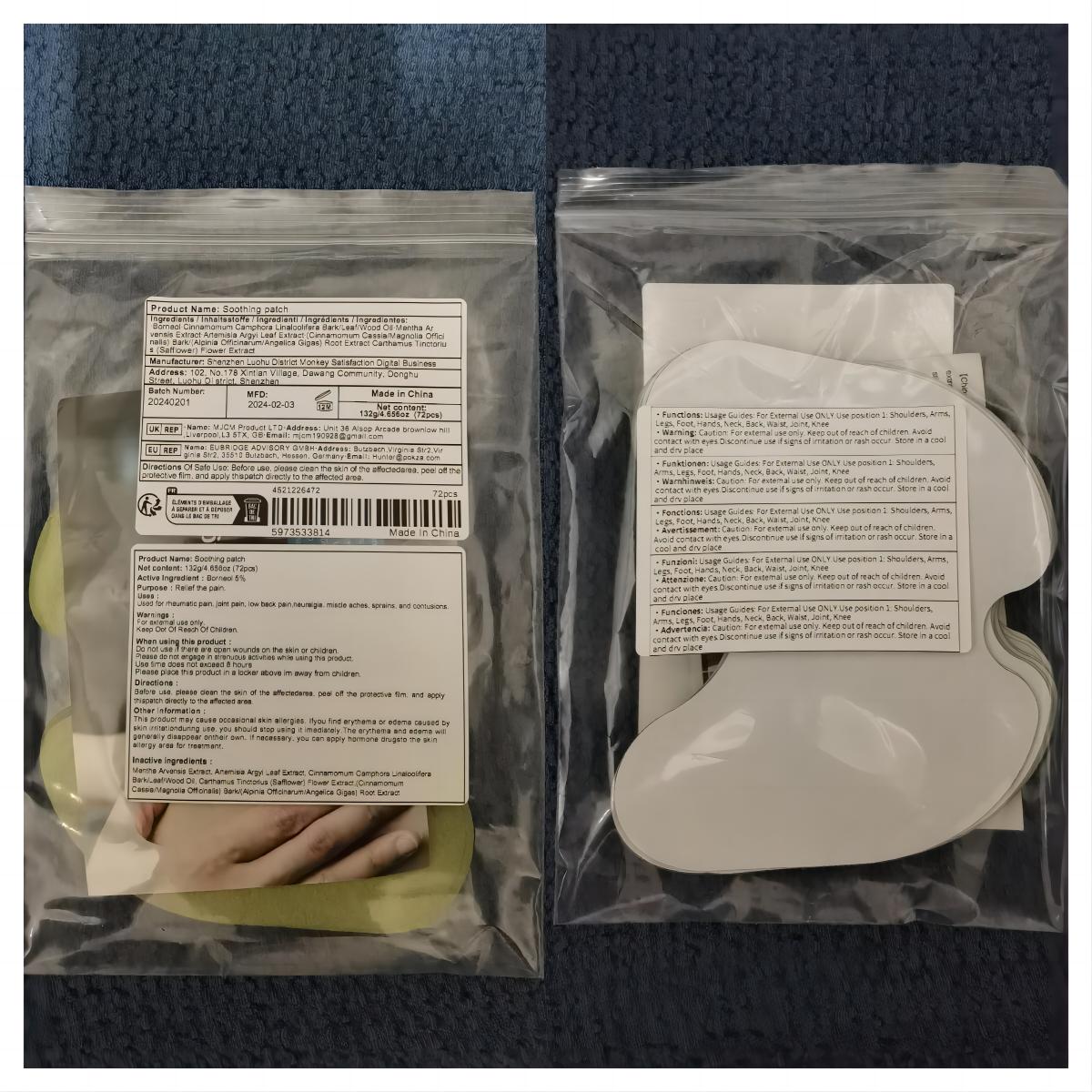 DRUG LABEL: Soothing patch
NDC: 83822-002 | Form: PATCH
Manufacturer: Fuzhou Ayimong Trading Co., Ltd.
Category: otc | Type: HUMAN OTC DRUG LABEL
Date: 20240225

ACTIVE INGREDIENTS: BORNEOL 5 g/100 1
INACTIVE INGREDIENTS: ARTEMISIA ARGYI LEAF; MENTHOL; CINNAMOMUM CAMPHORA WHOLE; CINNAMOMUM CASSIA TWIG; SAFFLOWER

83822-002

Active Ingredient

Borneol 5%

Purpose

Relief the pain.

Use

Used for rheumatic pain, joint pain, low back pain,neuralgia. miscle aches, sprains, and contusions.

Warnings

For external use only.

Do not use if there are open wounds on the skin or children.

When Using

Please do not engage in strenuous activities while using this product.

Stop Use

Use time does not exceed 8 hours

Keep Oot Of Reach Of Children

Please place this product in a locker above im away from children.

Directions

Before use, please clean the skin of the affectedarea, peel off the protective film, and apply thispatch directly to the affected area.

Other information

This product may cause occasional skin allergies. Ifyou find erythema or edema caused by skin irritationduring use, you should stop using it imediately.The erythema and edema will generally disappear ontheir own. If necessary, you can apply hormone drugsto the skin allergy area for treatment.

Inactive ingredients

Mentha Arvensis Extract, Artemisia Argyi Leaf Extract, Cinnamomum Camphora Linaloolifera Bark/Leaf/Wood Oil, Carthamus Tinctorius (Safflower) Flower Extract,(Cinnamomum Cassia/Magnolia Officinalis) Bark/(Alpinia Officinarum/Angelica Gigas) Root Extract